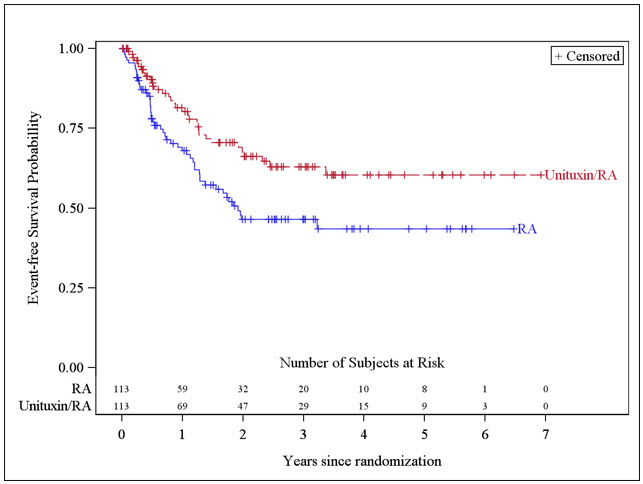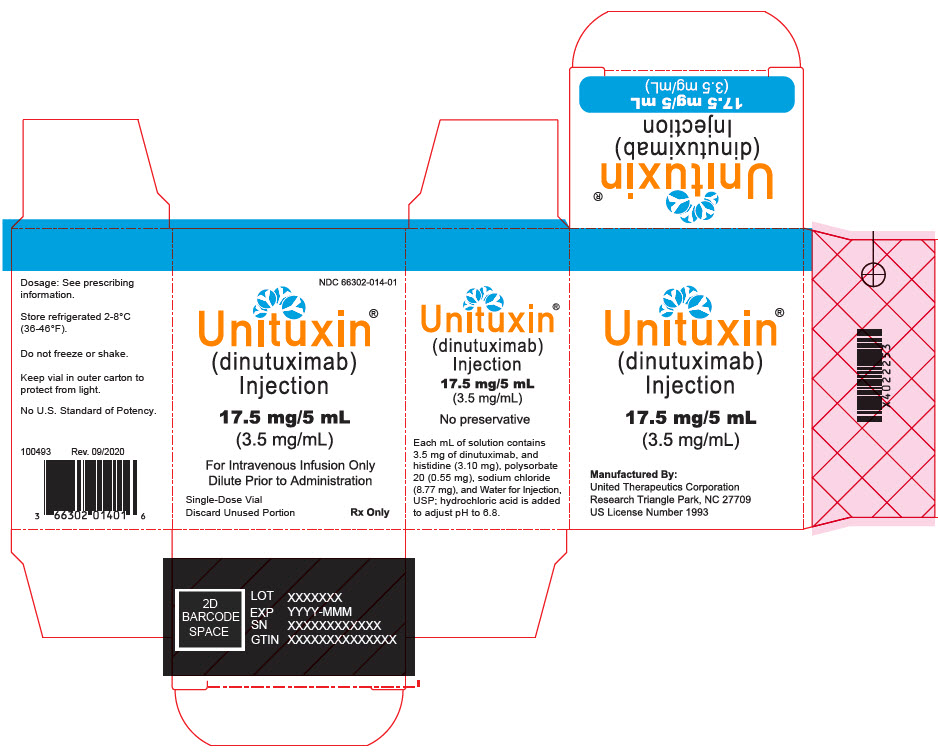 DRUG LABEL: Unituxin
NDC: 66302-014 | Form: INJECTION
Manufacturer: United Therapeutics Corporation
Category: prescription | Type: HUMAN PRESCRIPTION DRUG LABEL
Date: 20251021

ACTIVE INGREDIENTS: DINUTUXIMAB 3.5 mg/1 mL
INACTIVE INGREDIENTS: HISTIDINE; POLYSORBATE 20; SODIUM CHLORIDE; WATER; HYDROCHLORIC ACID

HIGHLIGHTS OF PRESCRIBING INFORMATION

These highlights do not include all the information needed to use UNITUXIN safely and effectively. See Full Prescribing Information for UNITUXIN.
UNITUXIN® (dinutuximab) injection, for intravenous use
Initial U.S. Approval: 2015

WARNING: SERIOUS INFUSION REACTIONS AND NEUROTOXICITY

See full prescribing information for complete boxed warning.

- Infusion Reactions: Life-threatening infusion adverse reactions occur with Unituxin. Administer required prehydration and premedication. Immediately interrupt for severe infusion reactions and permanently discontinue for anaphylaxis [see Dosage and Administration (2.2, 2.3) and Warnings and Precautions (5.1)].
- Neurotoxicity: Unituxin causes severe neuropathic pain. Administer intravenous opioid prior to, during, and for 2 hours following completion of the Unituxin infusion. Severe peripheral sensory neuropathy ranged from 2% to 9% in patients with neuroblastoma. Severe peripheral motor neuropathy has also been reported. Discontinue for severe unresponsive pain, severe sensory neuropathy, and moderate to severe peripheral motor neuropathy [see Dosage and Administration (2.2, 2.3) and Warnings and Precautions (5.2)].

RECENT MAJOR CHANGES

Dosage and Administration (2.3) | 10/2025

1 INDICATIONS AND USAGE

Unituxin is a GD2-binding monoclonal antibody indicated, in combination with granulocyte-macrophage colony-stimulating factor (GM-CSF), interleukin-2 (IL-2), and 13-cis-retinoic acid (RA), for the treatment of pediatric patients with high-risk neuroblastoma who achieve at least a partial response to prior first-line multiagent, multimodality therapy. (1)

2 DOSAGE AND ADMINISTRATION

- 17.5 mg/m^2/day as a diluted intravenous infusion over 10 to 20 hours for 4 consecutive days for up to 5 cycles. (2.1, 2.4)

3 DOSAGE FORMS AND STRENGTHS

- Injection: 17.5 mg/5 mL (3.5 mg/mL) in a single-dose vial. (3)

4 CONTRAINDICATIONS

- History of anaphylaxis to dinutuximab. (4)

5 WARNINGS AND PRECAUTIONS

- Neurological Disorders of the Eye: Interrupt Unituxin for dilated pupil with sluggish light reflex or other visual disturbances and permanently discontinue Unituxin for recurrent eye disorders or loss of vision. (5.2)
- Prolonged Urinary Retention and Transverse Myelitis: Permanently discontinue Unituxin and institute supportive care. (5.2)
- Reversible Posterior Leukoencephalopathy Syndrome (RPLS): Permanently discontinue Unituxin and institute supportive care for signs and symptoms of RPLS. (5.2)
- Capillary Leak Syndrome and Hypotension: Administer required prehydration and monitor patients closely during treatment. Depending upon severity, manage by interruption, infusion rate reduction, or permanent discontinuation. (5.3, 5.4)
- Infection: Interrupt until resolution of systemic infection. (5.5)
- Bone Marrow Suppression: Monitor peripheral blood counts during Unituxin therapy. (5.6)
- Electrolyte Abnormalities: Monitor serum electrolytes closely. (5.7)
- Atypical Hemolytic Uremic Syndrome: Permanently discontinue Unituxin and institute supportive management. (5.8)
- Embryo-Fetal Toxicity: May cause fetal harm. Advise females of reproductive potential of potential risk to a fetus and to use effective contraception. (5.9, 8.1, 8.3)

6 ADVERSE REACTIONS

The most common adverse drug reactions (≥25%) are pain, pyrexia, thrombocytopenia, lymphopenia, infusion reactions, hypotension, hyponatremia, increased alanine aminotransferase, anemia, vomiting, diarrhea, hypokalemia, capillary leak syndrome, neutropenia, urticaria, hypoalbuminemia, increased aspartate aminotransferase, and hypocalcemia. (5, 6.1)

The most common serious adverse reactions (≥5%) are infections, infusion reactions, hypokalemia, hypotension, pain, fever, and capillary leak syndrome. (5, 6.1)

To report SUSPECTED ADVERSE REACTIONS, contact United Therapeutics Corp. at 1-866-458-6479 or FDA at 1-800-FDA-1088 or www.fda.gov/medwatch.

FULL PRESCRIBING INFORMATION

WARNING: SERIOUS INFUSION REACTIONS AND NEUROTOXICITY

Infusion Reactions

- Serious and potentially life-threatening infusion reactions occurred in 26% of patients treated with Unituxin. Administer required prehydration and premedication including antihistamines prior to each Unituxin infusion. Monitor patients closely for signs and symptoms of an infusion reaction during and for at least four hours following completion of each Unituxin infusion. Immediately interrupt Unituxin for severe infusion reactions and permanently discontinue Unituxin for anaphylaxis (2.2, 2.3, 5.1).

Neurotoxicity

- Unituxin causes serious neurologic adverse reactions including severe neuropathic pain and peripheral neuropathy.
  Severe neuropathic pain occurs in the majority of patients. Administer intravenous opioid prior to, during, and for 2 hours following completion of the Unituxin infusion.
  In clinical studies of patients with high-risk neuroblastoma, Grade 3 peripheral sensory neuropathy occurred in 2% to 9% of patients. In clinical studies of Unituxin and related GD2-binding antibodies, severe motor neuropathy has occurred. Resolution of motor neuropathy did not occur in all cases. Discontinue Unituxin for severe unresponsive pain, severe sensory neuropathy, and moderate to severe peripheral motor neuropathy (2.2, 2.3, 5.2).

1 INDICATIONS AND USAGE

Unituxin (dinutuximab) is indicated, in combination with granulocyte-macrophage colony-stimulating factor (GM-CSF), interleukin-2 (IL-2), and 13-cis-retinoic acid (RA), for the treatment of pediatric patients with high-risk neuroblastoma who achieve at least a partial response to prior first-line multiagent, multimodality therapy [see Clinical Studies (14)].

2 DOSAGE AND ADMINISTRATION

- Verify that patients have adequate hematologic, respiratory, hepatic, and renal function prior to initiating each course of Unituxin [see Clinical Studies (14)].
- Administer required premedication and hydration prior to initiation of each Unituxin infusion [see Dosage and Administration (2.2)].

2.1 Recommended Dose

- The recommended dose of Unituxin is 17.5 mg/m^2/day administered as an intravenous infusion over 10 to 20 hours for 4 consecutive days for a maximum of 5 cycles (Table 1 and Table 2) [see Dosage and Administration (2.4) and Clinical Studies (14)].
- Initiate at an infusion rate of 0.875 mg/m^2/hour for 30 minutes. The infusion rate can be gradually increased as tolerated to a maximum rate of 1.75 mg/m^2/hour. Follow dose modification instructions for adverse reactions [see Dosage and Administration (2.3)].

Table 1: Schedule of Unituxin Administration for Cycles 1, 3, and 5
Cycle Day | 1 through 3 | 4 | 5 | 6 | 7 | 8 through 24 [Cycles 1, 3, and 5 are 24 days in duration.]
Unituxin |  | X | X | X | X

Table 2: Schedule of Unituxin Administration for Cycles 2 and 4
Cycle Day | 1 through 7 | 8 | 9 | 10 | 11 | 12 through 32 [Cycles 2 and 4 are 32 days in duration.]
Unituxin |  | X | X | X | X

2.2 Required Pre-treatment Guidelines

Intravenous Hydration

- Administer 0.9% Sodium Chloride Injection, USP 10 mL/kg as an intravenous infusion over 1 hour just prior to initiating each Unituxin infusion.

Analgesics

- Administer morphine sulfate (50 mcg/kg) intravenously immediately prior to initiation of Unituxin and then continue as a morphine sulfate drip at an infusion rate of 20 to 50 mcg/kg/hour during and for 2 hours following completion of Unituxin.
- Administer additional 25 mcg/kg to 50 mcg/kg intravenous doses of morphine sulfate as needed for pain up to once every 2 hours followed by an increase in the morphine sulfate infusion rate in clinically stable patients.
- Consider using fentanyl or hydromorphone if morphine sulfate is not tolerated.
- If pain is inadequately managed with opioids, consider use of gabapentin or lidocaine in conjunction with intravenous morphine.

Antihistamines and Antipyretics

- Administer an antihistamine such as diphenhydramine (0.5 to 1 mg/kg; maximum dose 50 mg) intravenously over 10 to 15 minutes starting 20 minutes prior to initiation of Unituxin and as tolerated every 4 to 6 hours during the Unituxin infusion.
- Administer acetaminophen (10 to 15 mg/kg; maximum dose 650 mg) 20 minutes prior to each Unituxin infusion and every 4 to 6 hours as needed for fever or pain. Administer ibuprofen (5 to 10 mg/kg) every 6 hours as needed for control of persistent fever or pain.

2.3 Dosage Modifications

Manage adverse reactions by infusion interruption, infusion rate reduction, dose reduction, or permanent discontinuation of Unituxin (Table 3 and Table 4) [see Warnings and Precautions (5), Adverse Reactions (6), and Clinical Studies (14)].

Table 3: Adverse Reactions Requiring Permanent Discontinuation of Unituxin

Grade 3 or 4 anaphylaxis

Grade 3 or 4 serum sickness

Grade 3 pain unresponsive to maximum supportive measures

Grade 4 sensory neuropathy or Grade 3 sensory neuropathy that interferes with daily activities for more than 2 weeks

Grade 2 or greater peripheral motor neuropathy

Urinary retention that persists following discontinuation of opioids

Transverse myelitis

Reversible posterior leukoencephalopathy syndrome (RPLS)

Subtotal or total vision loss

Grade 4 hyponatremia despite appropriate fluid management

Atypical hemolytic uremic syndrome

Table 4: Dose Modification for Selected Unituxin Adverse Reactions
Infusion-related reactions [see Warnings and Precautions (5.1)]
Mild to moderate adverse reactions, such as transient rash, fever, rigors, and localized urticaria, that respond promptly to symptomatic treatment
Onset of reaction: | Reduce Unituxin infusion rate to 50% of the previous rate and monitor closely.
After resolution: | Gradually increase infusion rate up to a maximum rate of 1.75 mg/m^2/hour.
Prolonged or severe adverse reactions, such as mild bronchospasm without other symptoms, or angioedema that does not affect the airway
Onset of reaction: | Immediately interrupt Unituxin.
After resolution: | If signs and symptoms resolve rapidly, resume Unituxin at 50% of the previous rate and observe closely.
First recurrence: | Discontinue Unituxin until the following day.; If symptoms resolve and continued treatment is warranted, premedicate with hydrocortisone 1 mg/kg (maximum dose 50 mg) intravenously and administer Unituxin at a rate of 0.875 mg/m^2/hour in an intensive care unit.
Second recurrence: | Permanently discontinue Unituxin.
Neurological disorders of the eye [see Warnings and Precautions (5.2)]
Onset of reaction: | Discontinue Unituxin infusion until resolution.
After resolution: | Reduce the Unituxin dose by 50%.
First recurrence or if accompanied by visual impairment: | Permanently discontinue Unituxin.
Capillary leak syndrome [see Warnings and Precautions (5.3)]
Moderate to severe but not life-threatening capillary leak syndrome
Onset of reaction: | Immediately interrupt Unituxin.
After resolution: | Resume Unituxin infusion at 50% of the previous rate.
Life-threatening capillary leak syndrome
Onset of reaction: | Discontinue Unituxin for the current cycle.
After resolution: | In subsequent cycles, administer Unituxin at 50% of the previous rate.
First recurrence: | Permanently discontinue Unituxin.
Hypotension [Symptomatic hypotension, systolic blood pressure (SBP) less than lower limit of normal for age, or SBP decreased by more than 15% compared to baseline.] requiring medical intervention [see Warnings and Precautions (5.4)]
Onset of reaction: | Interrupt Unituxin infusion.
After resolution: | Resume Unituxin infusion at 50% of the previous rate.; If blood pressure remains stable for at least 2 hours, increase the infusion rate as tolerated up to a maximum rate of 1.75 mg/m^2/hour.
Severe systemic infection or sepsis [see Warnings and Precautions (5.5)]
Onset of reaction: | Discontinue Unituxin until resolution of infection, and then proceed with subsequent cycles of therapy.

2.4 Instructions for Preparation and Administration

Preparation

- Store vials in a refrigerator at 2°C to 8°C (36°F to 46°F). Protect from light by storing in the outer carton. DO NOT FREEZE OR SHAKE vials.
- Inspect visually for particulate matter and discoloration prior to administration. Do not administer Unituxin and discard the single-dose vial if the solution is cloudy, has pronounced discoloration, or contains particulate matter.
- Aseptically withdraw the required volume of Unituxin from the single-dose vial and inject into a 100-mL bag of 0.9% Sodium Chloride Injection, USP. Mix by gentle inversion. Do not shake. Discard unused contents of the vial.
- Store the diluted Unituxin solution under refrigeration (2°C to 8°C). Initiate infusion within 4 hours of preparation.
- Discard diluted Unituxin solution 24 hours after preparation.

Administration

- Administer Unituxin as a diluted intravenous infusion only [see Dosage and Administration (2.1)]. Do not administer Unituxin as an intravenous push or bolus.

3 DOSAGE FORMS AND STRENGTHS

Injection: 17.5 mg/5 mL (3.5 mg/mL) as a clear and colorless to slightly opalescent solution in a single-dose vial.

4 CONTRAINDICATIONS

Unituxin is contraindicated in patients with a history of anaphylaxis to dinutuximab.

5 WARNINGS AND PRECAUTIONS

5.1 Serious Infusion Reactions

Serious infusion reactions requiring urgent intervention, including blood pressure support, bronchodilator therapy, corticosteroids, infusion rate reduction, infusion interruption, or permanent discontinuation of Unituxin, included facial and upper airway edema, dyspnea, bronchospasm, stridor, urticaria, and hypotension. Infusion reactions generally occurred during or within 24 hours of completing the Unituxin infusion. Due to overlapping signs and symptoms, it was not possible to distinguish between infusion reactions and hypersensitivity reactions in some cases.

In Study 1, Severe (Grade 3 or 4) infusion reactions occurred in 35 (26%) patients in the Unituxin/13-cis-retinoic acid (RA) group compared to 1 (1%) patient receiving RA alone. Severe urticaria occurred in 17 (13%) patients in the Unituxin/RA group but did not occur in the RA group. Serious adverse reactions consistent with anaphylaxis and resulting in permanent discontinuation of Unituxin occurred in 2 (1%) patients in the Unituxin/RA group. Additionally, 1 (0.1%) patient had multiple cardiac arrests and died within 24 hours after having received Unituxin in Study 2.

Prior to each Unituxin dose, administer required intravenous hydration and premedication with antihistamines, analgesics, and antipyretics [see Dosage and Administration (2.2)]. Monitor patients closely for signs and symptoms of infusion reactions during and for at least 4 hours following completion of each Unituxin infusion in a setting where cardiopulmonary resuscitation medication and equipment are available.

For mild to moderate infusion reactions, such as transient rash, fever, rigors, and localized urticaria, that respond promptly to antihistamines or antipyretics, decrease the Unituxin infusion rate and monitor closely. Immediately interrupt or permanently discontinue Unituxin and institute supportive management for severe or prolonged infusion reactions. Permanently discontinue Unituxin and institute supportive management for life-threatening infusion reactions [see Dosage and Administration (2.3)].

5.2 Neurotoxicity

Pain

In Study 1, 114 (85%) patients treated in the Unituxin/RA group experienced pain despite pre-treatment with analgesics, including morphine sulfate infusion. Severe (Grade 3) pain occurred in 68 (51%) patients in the Unituxin/RA group compared to 5 (5%) patients in the RA group. Pain typically occurred during the Unituxin infusion and was most commonly reported as abdominal pain, generalized pain, extremity pain, back pain, neuralgia, musculoskeletal chest pain, and arthralgia.

Premedicate with analgesics, including intravenous opioids, prior to each dose of Unituxin and continue analgesics until 2 hours following completion of Unituxin [see Dosage and Administration (2.2)].

For severe pain, decrease the Unituxin infusion rate to 0.875 mg/m^2/hour. Discontinue Unituxin if pain is not adequately controlled despite infusion rate reduction and institution of maximum supportive measures [see Dosage and Administration (2.3)].

Peripheral Neuropathy

In Study 1, severe (Grade 3) peripheral sensory neuropathy occurred in 2 (1%) patients and severe peripheral motor neuropathy occurred in 2 (1%) patients in the Unituxin/RA group. No patients treated with RA alone experienced severe peripheral neuropathy. The duration and reversibility of peripheral neuropathy occurring in Study 1 was not documented. In Study 3, no patients experienced peripheral motor neuropathy. Among the 9 (9%) patients who experienced peripheral sensory neuropathy of any severity, the median (min, max) duration of peripheral sensory neuropathy was 9 (3, 163) days.

In a study of a related anti-GD2 antibody conducted in 12 adult patients with metastatic melanoma, 2 (13%) patients developed severe motor neuropathy. One patient developed lower extremity weakness and inability to ambulate that persisted for approximately 6 weeks. Another patient developed severe lower extremity weakness resulting in an inability to ambulate without assistance that lasted for approximately 16 weeks and neurogenic bladder that lasted for approximately 3 weeks. Complete resolution of motor neuropathy was not documented in this case.

Permanently discontinue Unituxin in patients with peripheral motor neuropathy of Grade 2 or greater severity, Grade 3 sensory neuropathy that interferes with daily activities for more than 2 weeks, or Grade 4 sensory neuropathy [see Dosage and Administration (2.3)].

Neurological Disorders of the Eye

Neurological disorders of the eye experienced by 2 or more patients treated with Unituxin in Studies 1, 2, or 3 included blurred vision, photophobia, mydriasis, fixed or unequal pupils, optic nerve disorder, eyelid ptosis, and papilledema.

In Study 1, 3 (2%) patients in the Unituxin/RA group experienced blurred vision, compared to no patients in the RA group. Diplopia, mydriasis, and unequal pupillary size occurred in 1 patient each in the Unituxin/RA group, compared to no patients in the RA group. The duration of eye disorders occurring in Study 1 was not documented. In Study 3, eye disorders occurred in 16 (15%) patients, and in 3 (3%) patients resolution of the eye disorder was not documented. Among the cases with documented resolution, the median duration of eye disorders was 4 days (range: 0, 221 days).

Interrupt Unituxin in patients experiencing dilated pupil with sluggish light reflex or other visual disturbances that do not cause visual loss. Upon resolution and if continued treatment with Unituxin is warranted, decrease the Unituxin dose by 50%. Permanently discontinue Unituxin in patients with recurrent signs or symptoms of an eye disorder following dose reduction and in patients who experience loss of vision [see Dosage and Administration (2.3)].

Prolonged Urinary Retention

Urinary retention that persists for weeks to months following discontinuation of opioids has occurred in patients treated with Unituxin. Permanently discontinue Unituxin in patients with urinary retention that does not resolve following discontinuation of opioids [see Dosage and Administration (2.3) and Postmarketing Experience (6.2)].

Transverse Myelitis

Transverse myelitis has occurred in patients treated with Unituxin. Promptly evaluate any patient with signs or symptoms of transverse myelitis, such as weakness, paresthesia, sensory loss, or incontinence. Permanently discontinue Unituxin in patients who develop transverse myelitis [see Dosage and Administration (2.3) and Postmarketing Experience (6.2)].

Reversible Posterior Leukoencephalopathy Syndrome

Reversible Posterior Leukoencephalopathy Syndrome (RPLS) has occurred in patients treated with Unituxin. Institute appropriate medical treatment and permanently discontinue Unituxin in patients with signs and symptoms of RPLS (eg, severe headache, hypertension, visual changes, lethargy, or seizures) [see Dosage and Administration (2.3) and Postmarketing Experience (6.2)].

5.3 Capillary Leak Syndrome

In Study 1, severe (Grade 3 to 5) capillary leak syndrome occurred in 31 (23%) patients in the Unituxin/RA group and in no patients treated with RA alone. Additionally, capillary leak syndrome was reported as a serious adverse reaction in 9 (6%) patients in the Unituxin/RA group and in no patients treated with RA alone. Immediately interrupt or discontinue Unituxin and institute supportive management in patients with symptomatic or severe capillary leak syndrome [see Dosage and Administration (2.3)].

5.4 Hypotension

In Study 1, severe (Grade 3 or 4) hypotension occurred in 22 (16%) patients in the Unituxin/RA group compared to no patients in the RA group.

Prior to each Unituxin infusion, administer required intravenous hydration. Closely monitor blood pressure during Unituxin treatment. Immediately interrupt or discontinue Unituxin and institute supportive management in patients with symptomatic hypotension, systolic blood pressure (SBP) less than lower limit of normal for age, or SBP that is decreased by more than 15% compared to baseline [see Dosage and Administration (2.2, 2.3)].

5.5 Infection

In Study 1, severe (Grade 3 or 4) bacteremia requiring intravenous antibiotics or other urgent intervention occurred in 17 (13%) patients in the Unituxin/RA group compared to 5 (5%) patients treated with RA alone. Sepsis occurred in 24 (18%) patients in the Unituxin/RA group and in 10 (9%) patients in the RA group.

Monitor patients closely for signs and symptoms of systemic infection and temporarily discontinue Unituxin in patients who develop systemic infection until resolution of the infection [see Dosage and Administration (2.3)].

5.6 Bone Marrow Suppression

In Study 1, severe (Grade 3 or 4) thrombocytopenia (39% vs. 25%), anemia (34% vs. 16%), neutropenia (34% vs. 13%), and febrile neutropenia (4% vs. 0 patients) occurred more commonly in patients in the Unituxin/RA group compared to patients treated with RA alone. Monitor peripheral blood counts closely during therapy with Unituxin.

5.7 Electrolyte Abnormalities

In Study 1, electrolyte abnormalities occurring in at least 25% of patients who received Unituxin/RA included hyponatremia, hypokalemia, and hypocalcemia. Severe (Grade 3 or 4) hypokalemia and hyponatremia occurred in 37% and 23% of patients in the Unituxin/RA group, respectively, compared to 2% and 4% of patients in the RA group. In a study of a related anti-GD2 antibody conducted in 12 adult patients with metastatic melanoma, 2 (13%) patients developed syndrome of inappropriate antidiuretic hormone secretion resulting in severe hyponatremia. Monitor serum electrolytes daily during therapy with Unituxin.

5.8 Atypical Hemolytic Uremic Syndrome

Hemolytic uremic syndrome in the absence of documented infection and resulting in renal insufficiency, electrolyte abnormalities, anemia, and hypertension occurred in 2 patients enrolled in Study 2 following receipt of the first cycle of Unituxin. Atypical hemolytic uremic syndrome recurred following rechallenge with Unituxin in 1 patient. Permanently discontinue Unituxin and institute supportive management for signs of hemolytic uremic syndrome [see Dosage and Administration (2.3)].

5.9 Embryo-Fetal Toxicity

Based on its mechanism of action, Unituxin may cause fetal harm when administered to a pregnant woman. Advise pregnant women of the potential risk to a fetus. Advise females of reproductive potential to use effective contraception during treatment, and for 2 months after the last dose of Unituxin [see Use in Specific Populations (8.1, 8.3) and Clinical Pharmacology (12.1)].

6 ADVERSE REACTIONS

The following adverse reactions are discussed in greater detail in other sections of the labeling:

- Serious Infusion Reactions [see Boxed Warning and Warnings and Precautions (5.1)]
- Neurotoxicity, including Pain, Peripheral Neuropathy, Neurological Disorders of the Eye, Prolonged Urinary Retention, Transverse Myelitis, and Reversible Posterior Leukoencephalopathy Syndrome [see Boxed Warning and Warnings and Precautions (5.2)]
- Capillary Leak Syndrome [see Warnings and Precautions (5.3)]
- Hypotension [see Warnings and Precautions (5.4)]
- Infection [see Warnings and Precautions (5.5)]
- Bone Marrow Suppression [see Warnings and Precautions (5.6)]
- Electrolyte Abnormalities [see Warnings and Precautions (5.7)]
- Atypical Hemolytic Uremic Syndrome [see Warnings and Precautions (5.8)]
- Embryo-Fetal Toxicity [see Warnings and Precautions (5.9)]

6.1 Clinical Trials Experience

Because clinical trials are conducted under widely varying conditions, adverse reaction rates observed in the clinical trials of a drug cannot be directly compared to rates in the clinical trials of another drug and may not reflect rates observed in clinical practice.

The data described below reflect exposure to Unituxin at the recommended dose and schedule in 1021 patients with high-risk neuroblastoma enrolled in an open-label, randomized (Study 1), or single-arm clinical trials (Study 2 and Study 3). Prior to enrollment, patients received therapy consisting of induction combination chemotherapy, maximum feasible surgical resection, myeloablative consolidation chemotherapy followed by autologous stem cell transplant, and radiation therapy to residual soft tissue disease. Patients received Unituxin in combination with granulocyte-macrophage colony-stimulating factor (GM-CSF), interleukin-2 (IL-2), and 13-cis-retinoic acid (RA). Treatment commenced within 95 days post autologous stem cell transplant in Study 1, within 210 days of autologous stem cell transplant in Study 2, and within 110 days of autologous stem cell transplant in Study 3.

Study 1

In a randomized, open-label, multicenter study (Study 1), 134 patients received Unituxin in combination with GM-CSF, IL-2, and RA (Unituxin/RA group), including 109 randomized patients and 25 patients with biopsy-proven residual disease who were non-randomly assigned to receive Unituxin. A total of 106 randomized patients received RA alone (RA group) [see Dosage and Administration (2) and Clinical Studies (14)]. Patients had a median age at enrollment of 3.8 years (range: 0.94 to 15.3 years), and were predominantly male (60%) and White (82%). In Study 1, adverse reactions of Grade 3 or greater severity were comprehensively collected, but adverse reactions of Grade 1 or 2 severity were collected sporadically and laboratory data were not comprehensively collected.

Approximately 71% of patients in the Unituxin/RA group and 77% of patients in the RA group completed planned treatment. The most common reason for premature discontinuation of study therapy was adverse reactions in the Unituxin/RA group (19%) and progressive disease (17%) in the RA group.

The most common adverse drug reactions (≥25%) in the Unituxin/RA group were pain, pyrexia, thrombocytopenia, lymphopenia, infusion reactions, hypotension, hyponatremia, increased alanine aminotransferase, anemia, vomiting, diarrhea, hypokalemia, capillary leak syndrome, neutropenia, urticaria, hypoalbuminemia, increased aspartate aminotransferase, and hypocalcemia. The most common serious adverse reactions (≥5%) in the Unituxin/RA group were infections, infusion reactions, hypokalemia, hypotension, pain, fever, and capillary leak syndrome.

Table 5 lists the adverse reactions reported in at least 10% of patients in the Unituxin/RA group for which there was a between group difference of at least 5% (all grades) or 2% (Grade 3 or greater severity).

Table 5: Selected Adverse Reactions Occurring in at Least 10% of Patients in the Unituxin/RA Group in Study 1
Adverse Reaction [Includes adverse reactions that occurred in at least 10% of patients in the Unituxin/RA group with at least a 5% (All Grades) or 2% (Grades 3 to 5) absolute higher incidence in the Unituxin/RA group compared to the RA group.] , [Adverse drug reactions were graded using CTCAE version 3.0.] | Unituxin/RA (N=134) |  | RA (N=106)
Adverse Reaction [Includes adverse reactions that occurred in at least 10% of patients in the Unituxin/RA group with at least a 5% (All Grades) or 2% (Grades 3 to 5) absolute higher incidence in the Unituxin/RA group compared to the RA group.] , [Adverse drug reactions were graded using CTCAE version 3.0.] | All Grades (%) | Grades 3 to 4 (%) | All Grades (%) | Grades 3 to 4 (%)
General Disorders and Administration Site Conditions
Pain [Includes preferred terms abdominal pain, abdominal pain upper, arthralgia, back pain, bladder pain, bone pain, chest pain, facial pain, gingival pain, infusion related reaction, musculoskeletal chest pain, myalgia, neck pain, neuralgia, oropharyngeal pain, pain, pain in extremity, and proctalgia.] | 85 | 51 | 16 | 6
Pyrexia | 72 | 40 | 27 | 6
Edema | 17 | 0 | 0 | 0
Blood and Lymphatic System Disorders [Based on investigator reported adverse reactions.]
Thrombocytopenia | 66 | 39 | 43 | 25
Lymphopenia | 62 | 51 | 36 | 20
Anemia | 51 | 34 | 22 | 16
Neutropenia | 39 | 34 | 16 | 13
Immune System Disorders
Infusion reactions | 60 | 25 | 9 | 1
Vascular Disorders
Hypotension | 60 | 16 | 3 | 0
Capillary leak syndrome [One Grade 5 adverse reaction.] | 40 | 23 | 1 | 0
Hemorrhage [Includes preferred terms gastrointestinal hemorrhage, hematochezia, rectal hemorrhage, hematemesis, upper gastrointestinal hemorrhage, hematuria, hemorrhage urinary tract, renal hemorrhage, epistaxis, respiratory tract hemorrhage, disseminated intravascular coagulation, catheter site hemorrhage, hemorrhage, and hematoma.] | 17 | 6 | 6 | 3
Hypertension | 14 | 2 | 7 | 1
Metabolism and Nutrition Disorders
Hyponatremia | 58 | 23 | 12 | 4
Hypokalemia | 43 | 37 | 4 | 2
Hypoalbuminemia | 33 | 7 | 3 | 0
Hypocalcemia | 27 | 7 | 0 | 0
Hypophosphatemia | 20 | 8 | 3 | 0
Hyperglycemia | 18 | 6 | 4 | 1
Hypertriglyceridemia | 16 | 1 | 11 | 1
Decreased appetite | 15 | 10 | 5 | 4
Hypomagnesemia | 12 | 2 | 1 | 0
Investigations
Increased alanine aminotransferase | 56 | 23 | 31 | 3
Increased aspartate aminotransferase | 28 | 10 | 7 | 0
Increased serum creatinine | 15 | 2 | 6 | 0
Increased weight | 10 | 0 | 0 | 0
Gastrointestinal Disorders
Vomiting | 46 | 6 | 19 | 3
Diarrhea | 43 | 13 | 15 | 1
Nausea | 10 | 2 | 3 | 1
Skin and Subcutaneous Tissue Disorders
Urticaria | 37 | 13 | 3 | 0
Respiratory, Thoracic and Mediastinal Disorders
Hypoxia | 24 | 12 | 2 | 1
Cardiac Disorders
Tachycardia [Includes preferred terms tachycardia and sinus tachycardia.] | 19 | 2 | 1 | 0
Infections and Infestations
Sepsis | 18 | 16 | 9 | 9
Device related infection | 16 | 16 | 11 | 11
Renal and Urinary Disorders
Proteinuria | 16 | 0 | 3 | 1
Nervous System Disorders
Peripheral neuropathy | 13 | 3 | 6 | 0

Table 6 compares the per-patient incidence of selected adverse reactions occurring during cycles containing Unituxin in combination with GM-CSF (Cycles 1, 3, and 5) with cycles containing Unituxin in combination with IL-2 (Cycles 2 and 4).

Table 6: Comparison of Adverse Events by Treatment Cycle in the Unituxin/RA Group in Study 1
Preferred Term [Includes preferred terms with a per-patient incidence of at least 20% in the Unituxin and RA group for either IL-2 or GM-CSF containing cycles.] , [Adverse drug reactions were graded using CTCAE version 3.0.] | All Grades |  | Severe
Preferred Term [Includes preferred terms with a per-patient incidence of at least 20% in the Unituxin and RA group for either IL-2 or GM-CSF containing cycles.] , [Adverse drug reactions were graded using CTCAE version 3.0.] | GM-CSF N=134 (%) | IL-2 [Seven patients who received GM-CSF in Cycle 1 discontinued prior to starting Cycle 2.] N=127 (%) | GM-CSF N=134 (%) | IL-2 N=127 (%)
General Disorders and administration site conditions
Pyrexia | 55 | 65 | 10 | 37
Pain [Includes preferred terms abdominal pain, abdominal pain upper, arthralgia, back pain, bladder pain, bone pain, chest pain, facial pain, gingival pain, infusion related reaction, musculoskeletal chest pain, myalgia, neck pain, neuralgia, oropharyngeal pain, pain, pain in extremity, and proctalgia.] | 77 | 61 | 43 | 35
Blood and Lymphatic System Disorders [Based on investigator-reported adverse reactions.]
Thrombocytopenia | 62 | 61 | 31 | 33
Lymphopenia | 54 | 61 | 33 | 50
Anemia | 42 | 42 | 21 | 24
Neutropenia | 25 | 32 | 19 | 28
Immune System Disorders
Infusion reactions | 47 | 54 | 10 | 20
Vascular Disorders
Hypotension | 43 | 54 | 5 | 16
Capillary leak syndrome | 22 | 36 | 11 | 20
Metabolism and Nutrition Disorders
Hyponatremia | 36 | 55 | 5 | 21
Hypokalemia | 26 | 39 | 13 | 33
Hypoalbuminemia | 29 | 29 | 3 | 5
Hypocalcemia | 20 | 21 | 2 | 6
Investigations
Increased alanine aminotransferase | 43 | 48 | 15 | 13
Aspartate aminotransferase increased | 16 | 21 | 4 | 7
Gastrointestinal Disorders
Diarrhea | 31 | 37 | 6 | 13
Vomiting | 33 | 35 | 3 | 2
Skin and Subcutaneous Tissue Disorders
Urticaria | 25 | 29 | 7 | 7
GM-CSF, granulocyte-macrophage colony-stimulating factor; IL-2, interleukin-2; RA, 13-cis-retinoic acid

Study 2 and Study 3

Study 2 was a single-arm, multicenter, expanded access trial that enrolled patients with high-risk neuroblastoma (N=783). The reported adverse event profile of Unituxin in Study 2 was similar to that observed in Study 1.

Study 3 was a multicenter, single-arm safety study of Unituxin in combination with GM-CSF, IL-2, and RA. In Study 3, adverse events of all CTCAE grades and laboratory data were systematically and comprehensively collected. Of 104 patients enrolled and treated in Study 3, 77% of patients completed study therapy. In general, the adverse reaction profile of Unituxin observed in Study 3 was similar to that observed in Study 1 and Study 2. The following adverse reactions not previously reported in Study 1 were reported in at least 10% of patients in Study 3: nasal congestion (20%) and wheezing (15%). Table 7 provides the per-patient incidence of laboratory abnormalities in Study 3.

Table 7: Per-patient Incidence of Selected (≥5% Grade 3 to 4) Laboratory Abnormalities in Study 3
Laboratory Test [Laboratory abnormalities with a per-patient incidence of at least 20% (all grades) and at least a 5% per-patient incidence of severe (Grade 3 or 4) laboratory abnormalities.] | Grade [Based on CTCAE version 4.0.]
Laboratory Test [Laboratory abnormalities with a per-patient incidence of at least 20% (all grades) and at least a 5% per-patient incidence of severe (Grade 3 or 4) laboratory abnormalities.] | All Grades % | Grades 3 to 4 %
Hematology
Anemia | 100 | 46
Neutropenia | 99 | 63
Thrombocytopenia | 98 | 49
Chemistry
Hypoalbuminemia | 100 | 8
Hypocalcemia | 97 | 7
Hyponatremia | 93 | 36
Hyperglycemia | 87 | 6
Aspartate Aminotransferase Increased | 84 | 8
Alanine Aminotransferase Increased | 83 | 13
Hypokalemia | 82 | 41
Hypophosphatemia | 78 | 6
Urinalysis [Urinalysis results were reported as positive or negative without assessment of grade.]
Urine protein | 66 | ND
Red blood cell casts | 38 | ND
ND, not determined

6.2 Postmarketing Experience

The following adverse reactions have been identified during post-approval use of Unituxin. Because these reactions are reported voluntarily from a population of uncertain size, it is not always possible to reliably estimate their frequency or establish a causal relationship to drug exposure.

- Neurotoxicity: prolonged urinary retention, transverse myelitis, and reversible posterior leukoencephalopathy syndrome (RPLS) [see Warnings and Precautions (5.2)].

7 DRUG INTERACTIONS

No drug-drug interaction studies have been conducted with dinutuximab.

8 USE IN SPECIFIC POPULATIONS

8.1 Pregnancy

Risk Summary

Based on its mechanism of action, Unituxin may cause fetal harm when administered to a pregnant woman [see Clinical Pharmacology (12.1)]. There are no studies in pregnant women and no reproductive studies in animals to inform the drug-associated risk. Monoclonal antibodies are transported across the placenta in a linear fashion as pregnancy progresses, with the largest amount transferred during the third trimester. Advise pregnant women of the potential risk to a fetus. The background risk of major birth defects and miscarriage for the indicated population is unknown. However, the background risk in the U.S. general population of major birth defects is 2 to 4% and of miscarriage is 15 to 20% of clinically recognized pregnancies.

8.2 Lactation

Risk Summary

There is no information available on the presence of dinutuximab in human milk, the effects of the drug on the breastfed infant, or the effects of the drug on milk production. However, human IgG is present in human milk. Because of the potential for serious adverse reactions in a breastfed infant, advise a nursing woman to discontinue breastfeeding during treatment with Unituxin.

8.3 Females and Males of Reproductive Potential

Contraception

Females

Unituxin may cause fetal harm [see Use in Specific Populations (8.1)]. Advise females of reproductive potential to use effective contraception during treatment and for 2 months after the last dose of Unituxin.

8.4 Pediatric Use

The safety and effectiveness of Unituxin as part of multi-agent, multimodality therapy have been established in pediatric patients with high-risk neuroblastoma based on results of an open-label, randomized (1:1) trial conducted in 226 patients aged 11 months to 15 years (median age 3.8 years) (Study 1). Prior to enrollment, patients achieved at least a partial response to prior first-line therapy for high-risk neuroblastoma consisting of induction combination chemotherapy, maximum feasible surgical resection, myeloablative consolidation chemotherapy followed by autologous stem cell transplant, and received radiation therapy to residual soft tissue disease. Patients randomized to the Unituxin/13-cis-retinoic acid (RA) arm (Unituxin/RA) received up to 5 cycles of Unituxin in combination with alternating cycles of granulocyte-macrophage colony-stimulating factor (GM-CSF) and interleukin-2 (IL-2) plus RA, followed by 1 cycle of RA alone. Patients randomized to the RA arm received up to 6 cycles of RA monotherapy. Study 1 demonstrated an improvement in event-free survival (EFS) and overall survival (OS) in patients in the Unituxin/RA arm compared to those in the RA arm [see Adverse Reactions (6), Clinical Pharmacology (12), and Clinical Studies (14)].

Juvenile Animal Toxicity Data

Juvenile monkeys (13 to 18 months of age at study start) received dinutuximab daily via intravenous infusion for 4 consecutive days over five 28-day cycles at doses of 1, 3, or 10 mg/kg. Monkeys also received morphine during infusion for pain management. At the high dose of 10 mg/kg (approximately equal to the 17.5 mg/m^2 clinical dose), mild degeneration of nerve fibers in the brain (medulla oblongata) and moderate degeneration of nerve fibers in the spinal cord (cervical, thoracic, and lumbar) were present. Mild neuronal and nerve fiber degeneration were also present in the dorsal root ganglia (cervical, thoracic, and lumbar). Nerve fiber degeneration in the spinal cord and neuronal degeneration in dorsal root ganglia persisted 6 months after the end of dosing, though at lower severity. At the 10 mg/kg dose level, nerve conduction velocity (NCV) analysis showed motor and sensory NCV decreases of less than 10% compared to vehicle controls, starting on Day 27 and continuing to Day 83. Sensory NCV decreases were still present at the end of the dosing period but were on a trend towards recovery 6 months after the end of dosing.

8.5 Geriatric Use

The safety and effectiveness of Unituxin in geriatric patients have not been established.

8.6 Renal Impairment

Unituxin has not been studied in patients with renal impairment.

8.7 Hepatic Impairment

Unituxin has not been studied in patients with hepatic impairment.

11 DESCRIPTION

Dinutuximab is a glycolipid disialoganglioside (GD2)-binding chimeric monoclonal antibody composed of murine variable heavy and light chain regions and the human constant region for the heavy chain IgG1 and light chain kappa. Dinutuximab is produced in the murine myeloma cell line, SP2/0 and has an approximate molecular weight of 150 kDa.

Unituxin (dinutuximab) injection is a sterile, preservative-free, clear and colorless to slightly opalescent solution for intravenous infusion. Unituxin is supplied in single-dose vials of 17.5 mg/5 mL. Each mL of solution contains 3.5 mg of dinutuximab, and histidine (3.10 mg), polysorbate 20 (0.55 mg), sodium chloride (8.77 mg), and Water for Injection, USP; hydrochloric acid is added to adjust pH to 6.8.

12 CLINICAL PHARMACOLOGY

12.1 Mechanism of Action

Dinutuximab binds to the glycolipid GD2. This glycolipid is expressed on neuroblastoma cells and on normal cells of neuroectodermal origin, including the central nervous system and peripheral nerves. Dinutuximab binds to cell surface GD2 and induces cell lysis of GD2-expressing cells through antibody-dependent cell-mediated cytotoxicity (ADCC) and complement-dependent cytotoxicity (CDC).

12.3 Pharmacokinetics

The pharmacokinetics of dinutuximab was evaluated by a population pharmacokinetic analysis in a clinical study of Unituxin in combination with GM-CSF, IL-2, and RA. In this study, 27 children with high-risk neuroblastoma (age: 3.9±1.9 years) received up to 5 cycles of Unituxin at 17.5 mg/m^2/day as an intravenous infusion over 10 to 20 hours for 4 consecutive days every 28 days. The observed maximum plasma dinutuximab concentration (Cmax) was 11.5 mcg/mL (20%, coefficient of variation [CV]). The mean volume of distribution at steady state (Vdss) was 5.4 L (28%). The clearance was 0.21 L/day (62%) and increased with body size. The terminal half-life was 10 days (56%).

No formal pharmacokinetic studies were conducted in patients with renal or hepatic impairment.

12.6 Immunogenicity

As with all therapeutic proteins, there is a potential for immunogenicity. The detection of antibody formation is highly dependent on the sensitivity and specificity of the assay. Additionally, the observed incidence of antibody (including neutralizing antibody) positivity in an assay may be influenced by several factors, including assay methodology, sample handling, timing of sample collection, concomitant medications, and underlying disease. For these reasons, comparison of the incidence of antibodies in the studies described below with the incidence of antibodies in other studies or to other products may be misleading.

Among the 418 patients who were treated with Unituxin in combination with GM-CSF, IL-2, and RA in Study 2, Study 3 and Study DIV-NB-201, 86 patients (20.6%) tested positive for anti-dinutuximab antibodies (ADA). Of the 86 ADA positive patients, 45 (52.3%) tested positive for neutralizing antibodies.

Among the 27 patients who were treated with Unituxin in combination with lenalidomide and isotretinoin in Study NANT 2011-04, 13 patients (48.1%) tested positive for ADA. Of the 13 ADA positive patients, 2 (15.4%) also tested positive for neutralizing antibodies.

The clearance of dinutuximab was 60% higher for the ADA positive patients than the ADA negative patients. The presence of ADA did not have a clinically significant effect on the incidence or severity of adverse reactions. There were insufficient number of patients with ADA to determine whether ADA alters the efficacy of Unituxin.

13 NONCLINICAL TOXICOLOGY

13.1 Carcinogenesis, Mutagenesis, Impairment of Fertility

No animal studies have been conducted to evaluate the carcinogenic or mutagenic potential of dinutuximab.

Dedicated studies examining the effects of dinutuximab on fertility in animals have not been conducted. No clear effects on reproductive organs were observed in general toxicology studies conducted in rats.

13.2 Animal Toxicology and/or Pharmacology

Nonclinical studies suggest that dinutuximab-induced neuropathic pain and neurotoxicity are mediated by binding of the antibody to the GD2 antigen located on the surface of nerve fibers and myelin and subsequent induction of CDC and ADCC activity.

14 CLINICAL STUDIES

The safety and effectiveness of Unituxin was evaluated in a randomized, open-label, multicenter trial conducted in pediatric patients with high-risk neuroblastoma (Study 1). All patients had received prior therapy consisting of induction combination chemotherapy, maximum feasible surgical resection, myeloablative consolidation chemotherapy followed by autologous stem cell transplant, and radiation therapy to residual soft tissue disease. Patients were randomized between Day 50 and Day 77 post-autologous stem cell transplantation.

Patients were required to have achieved at least a partial response prior to autologous stem cell transplantation, have no evidence of disease progression following completion of front-line multi-modality therapy, have adequate pulmonary function (no dyspnea at rest and peripheral arterial oxygen saturation of at least 94% on room air), adequate hepatic function (total bilirubin <1.5× the upper limit of normal and ALT <5× the upper limit of normal), adequate cardiac function (shortening fraction of >30% by echocardiogram, or if shortening fraction abnormal, ejection fraction of 55% by gated radionuclide study), and adequate renal function (glomerular filtration rate at least 70 mL/min/1.73 m^2). Patients with systemic infections or a requirement for concomitant systemic corticosteroids or immunosuppressant usage were not eligible for enrollment.

Patients randomized to the Unituxin/RA arm received up to 5 cycles of Unituxin (clinical trials material) in combination with granulocyte-macrophage colony-stimulating factor (GM-CSF) (Table 8) or interleukin-2 (IL-2) (Table 9) plus 13-cis-retinoic acid (RA), followed by 1 cycle of RA alone. Patients randomized to the RA arm received 6 cycles of RA. Unituxin was administered at a dose of 17.5 mg/m^2/day (equivalent to 25 mg/m^2/day of clinical trials material) on 4 consecutive days. Patients in both treatment arms received 6 cycles of RA at a dose of 160 mg/m^2/day orally (for patients weighing more than 12 kg) or 5.33 mg/kg/day (for patients weighing less than or equal to 12 kg) in 2 divided doses for 14 consecutive days.

Table 8: Dosage Regimen in the Unituxin/RA Arm for Cycles 1, 3, and 5
Cycle Day | 1 | 2 | 3 | 4 | 5 | 6 | 7 | 8 | 9 | 10 | 11 | 12 | 13 | 14 | 15-24
GM-CSF [GM-CSF: 250 µg/m^2/day, administered by either subcutaneous injection (recommended) or IV infusion administered over 2 hours.] | X | X | X | X | X | X | X | X | X | X | X | X | X | X
Unituxin [Unituxin: 17.5 mg/m^2/day, administered by diluted IV infusion over 10 to 20 hours.] |  |  |  | X | X | X | X
RA [RA: for >12 kg body weight, 80 mg/m^2 orally twice daily for a total dose of 160 mg/m^2/day; for ≤12 kg body weight, 2.67 mg/kg orally twice daily for a total daily dose of 5.33 mg/kg/day (round dose up to nearest 10 mg).] |  |  |  |  |  |  |  |  |  |  | X | X | X | X | X

Table 9: Dosage Regimen in the Unituxin/RA Arm for Cycles 2 and 4
Cycle Day | 1 | 2 | 3 | 4 | 5 | 6 | 7 | 8 | 9 | 10 | 11 | 12-14 | 15-28 | 29-32
IL-2 [IL-2: 3 MIU/m^2/day administered by continuous IV infusion over 96 hours on Days 1 to 4 and 4.5 MIU/m^2/day on Days 8 to 11.] | X | X | X | X |  |  |  | X | X | X | X
Unituxin [Unituxin: 17.5 mg/m^2/day, administered by diluted IV infusion over 10 to 20 hours.] |  |  |  |  |  |  |  | X | X | X | X
RA [RA: for >12 kg body weight, 80 mg/m^2 orally twice daily for a total dose of 160 mg/m^2/day; for ≤12 kg body weight, 2.67 mg/kg orally twice daily for a total daily dose of 5.33 mg/kg/day (round dose up to nearest 10 mg).] |  |  |  |  |  |  |  |  |  |  |  |  | X

A total of 226 patients were randomized, 113 patients to each arm. In general, demographic and baseline tumor characteristics were similar across study arms. Across the study population, 60% were male, the median age was 3.8 years and 3% of patients were less than 1.5 years, 82% were White and 7% were Black. The majority (80%) of patients had International Neuroblastoma Staging System Stage 4 disease. Thirty-five percent of patients had a complete response, 43% had a very good partial response, and 23% had a partial response to therapy received prior to autologous stem cell transplant. Forty-six percent of patients had neuroblastoma that was not MYCN-amplified, 36% had tumors with known MYCN-amplification, and MYCN status was unknown or missing in 19% of patients. Forty-three percent of patients had hyperdiploid tumors, 36% had diploid tumors, and DNA ploidy status was unknown or missing in 21% of patients.

The major efficacy outcome measure was investigator-assessed event-free survival (EFS), defined as the time from randomization to the first occurrence of relapse, progressive disease, secondary malignancy, or death. Overall survival (OS) was also evaluated. After observing a numerical improvement in EFS based on the seventh interim analysis, the Data Monitoring Committee recommended termination of accrual. Efficacy results are shown in Table 10.

Table 10: Efficacy Results
Efficacy Parameter |  | Unituxin/RA arm n=113 | RA arm n=113
EFS | No. of Events (%) | 33 (29%) | 50 (44%)
EFS | Median (95% CI) (years) | NR (3.4, NR) | 1.9 (1.3, NR)
EFS | Hazard Ratio (95% CI) | 0.57 (0.37, 0.89)
EFS | p-value (log-rank test) [Compared to the allocated alpha of 0.01 pre-specified for the seventh interim analysis of EFS] | 0.01
OS [Based on an additional 3 years of follow up after the seventh interim analysis of EFS] | No. of Events (%) | 31 (27%) | 48 (42%)
OS [Based on an additional 3 years of follow up after the seventh interim analysis of EFS] | Median (95% CI) (years) | NR (7.5, NR) | NR (3.9, NR)
OS [Based on an additional 3 years of follow up after the seventh interim analysis of EFS] | Hazard Ratio (95% CI) | 0.58 (0.37, 0.91)
NR, not reached

The Kaplan-Meier curve of EFS is shown in Figure 1.

Figure 1: Kaplan-Meier Curve of Event-Free Survival

16 HOW SUPPLIED/STORAGE AND HANDLING

Unituxin (dinutuximab) injection as a clear and colorless to slightly opalescent solution is supplied in a carton containing one 17.5 mg/5 mL (3.5 mg/mL) single-dose vial.

NDC 66302-014-01

STORAGE AND HANDLING

Store Unituxin vials under refrigeration at 2°C to 8°C (36°F to 46°F) in the outer carton to protect from light until time of use. Do not freeze or shake the vial.

17 PATIENT COUNSELING INFORMATION

- Serious Infusion Reactions
  Inform patients and caregivers of the risk of serious infusion reactions and anaphylaxis and to immediately report any signs or symptoms, such as facial or lip swelling, urticaria, difficulty breathing, lightheadedness, or dizziness that occur during or within 24 hours following the infusion [see Warnings and Precautions (5.1)].
- Pain, Peripheral Neuropathy, Prolonged Urinary Retention, and Transverse Myelitis
  Inform patients and caregivers of the risk of severe pain, sensory and motor neuropathy, prolonged urinary retention, and transverse myelitis, and to promptly report severe or worsening pain and signs and symptoms, such as numbness, tingling, burning, weakness, or inability to urinate [see Warnings and Precautions (5.2)].
- Neurological Disorders of the Eye
  Inform patients and caregivers of the risk of neurological disorders of the eye and to promptly report signs or symptoms, such as blurred vision, photophobia, ptosis, diplopia, or unequal pupil size [see Warnings and Precautions (5.2)].
- Reversible Posterior Leukoencephalopathy Syndrome (RPLS)
  Inform patients and caregivers of the risk of RPLS and to immediately report signs or symptoms, such as severe headache, hypertension, visual changes, lethargy, or seizures [see Warnings and Precautions (5.2)].
- Capillary Leak Syndrome
  Inform patients and caregivers of the risk of capillary leak syndrome and to immediately report any signs or symptoms [see Warnings and Precautions (5.3)].
- Hypotension
  Inform patients and caregivers of the risk of hypotension during the infusion and to immediately report any signs or symptoms [see Warnings and Precautions (5.4)].
- Infection
  Inform patients and caregivers of the risk of infection following treatment and to immediately report any signs or symptoms [see Warnings and Precautions (5.5)].
- Bone Marrow Suppression
  Inform patients and caregivers of the risk of bone marrow suppression, and to promptly report signs or symptoms of anemia, thrombocytopenia, or infection [see Warnings and Precautions (5.6)].
- Electrolyte Abnormalities
  Inform patients and caregivers of the risk of electrolyte abnormalities, including hypokalemia, hyponatremia, and hypocalcemia, and to report any signs or symptoms, such as seizures, heart palpitations, and muscle cramping [see Warnings and Precautions (5.7)].
- Atypical Hemolytic Uremic Syndrome
  Inform patients and caregivers of the risk of hemolytic uremic syndrome and to report any signs or symptoms, such as fatigue, dizziness, fainting, pallor, edema, decreased urine output, or hematuria [see Warnings and Precautions (5.8)].
- Embryo-Fetal Toxicity
  Advise women of reproductive potential of the potential risk to the fetus if administered during pregnancy and the need for use of effective contraception during and for at least 2 months after completing therapy [see Warnings and Precautions (5.9)].

®Copyright 2025 United Therapeutics Corp. All rights reserved.

Unituxin manufactured by:

United Therapeutics Corp.
Durham, NC 27713
US License No. 1993

PRINCIPAL DISPLAY PANEL - 5 mL Vial Box

NDC 66302-014-01

Unituxin®
(dinutuximab)
Injection

17.5 mg/5 mL
(3.5 mg/mL)

For Intravenous Infusion Only
Dilute Prior to Administration

Single-Dose Vial
Discard Unused Portion
Rx Only